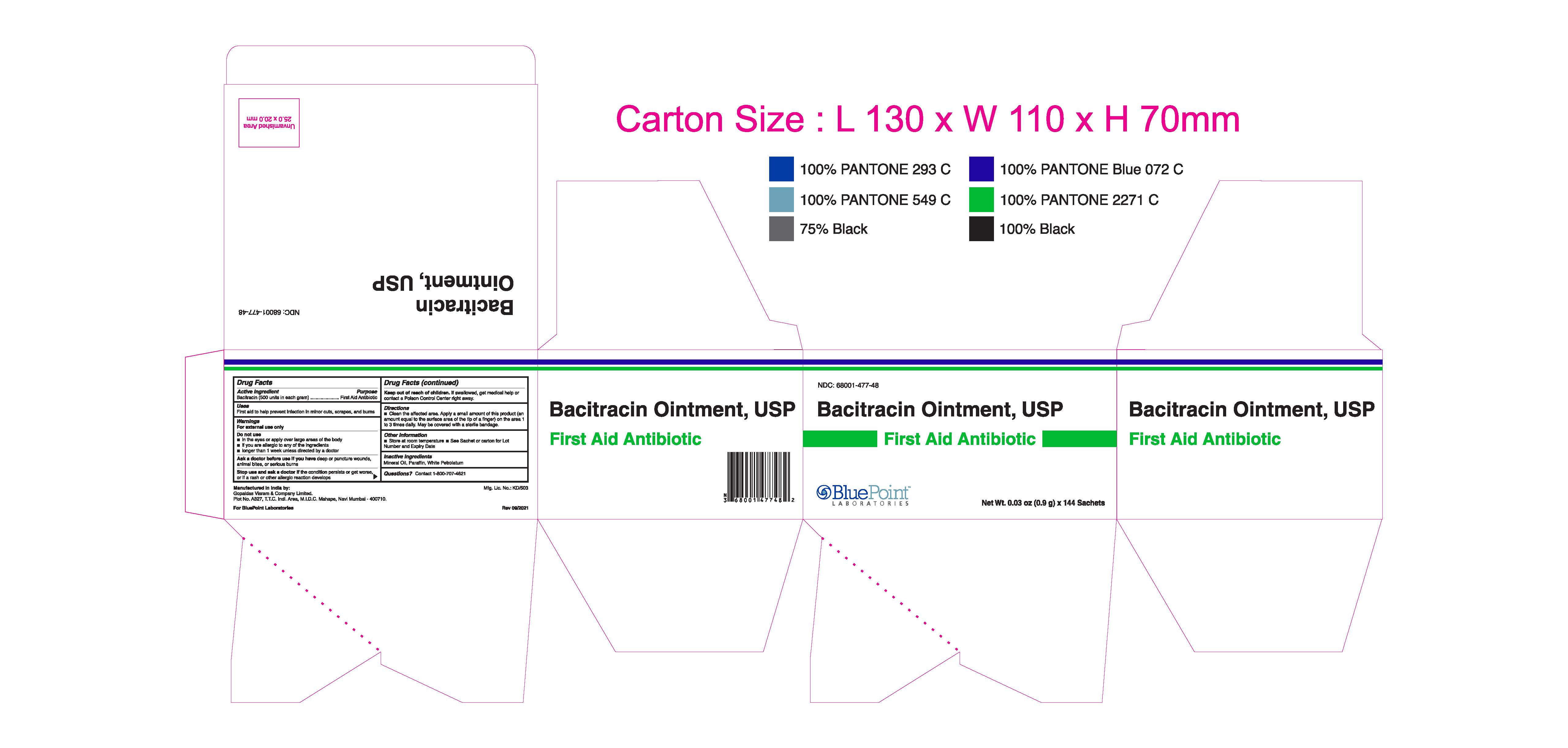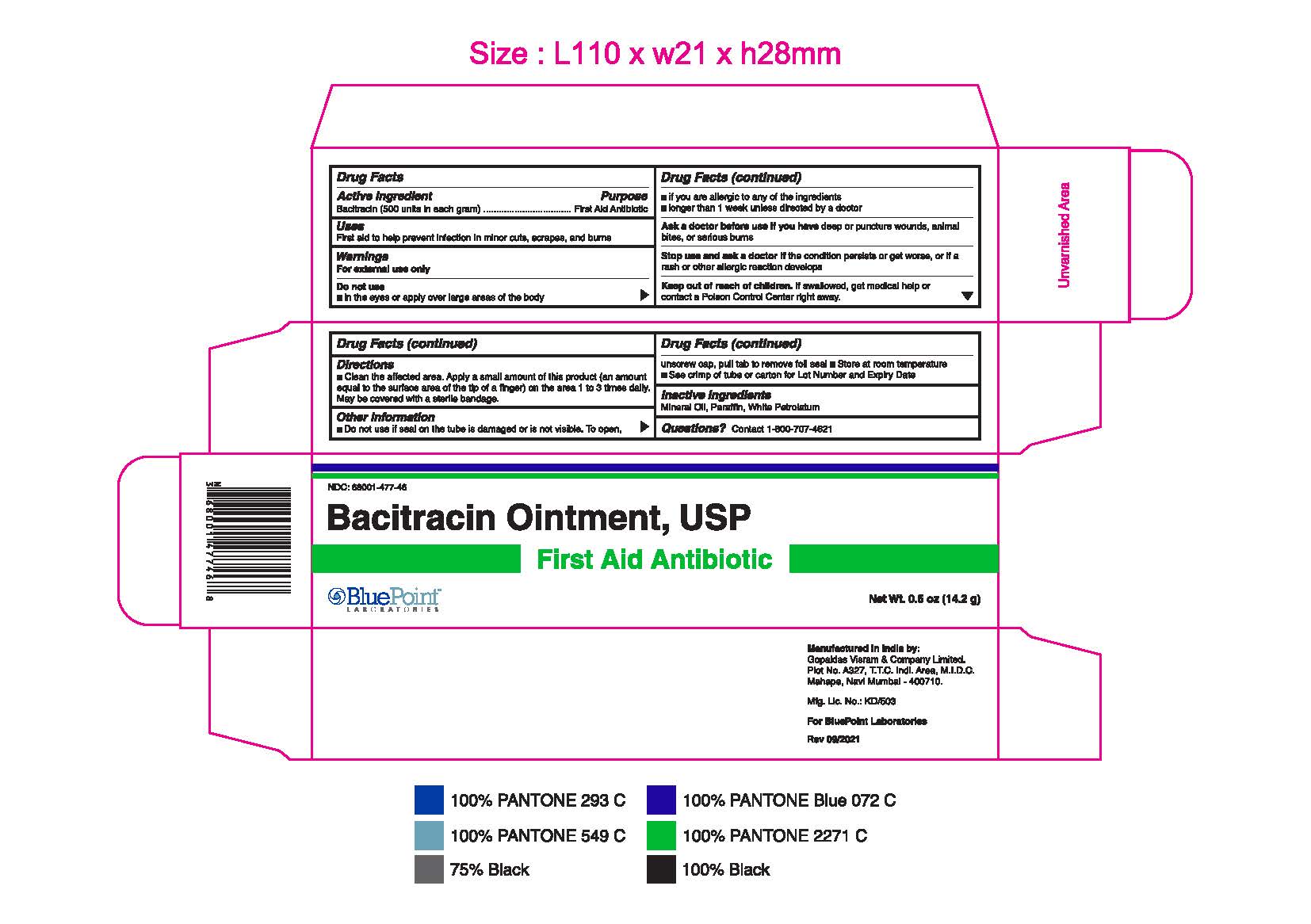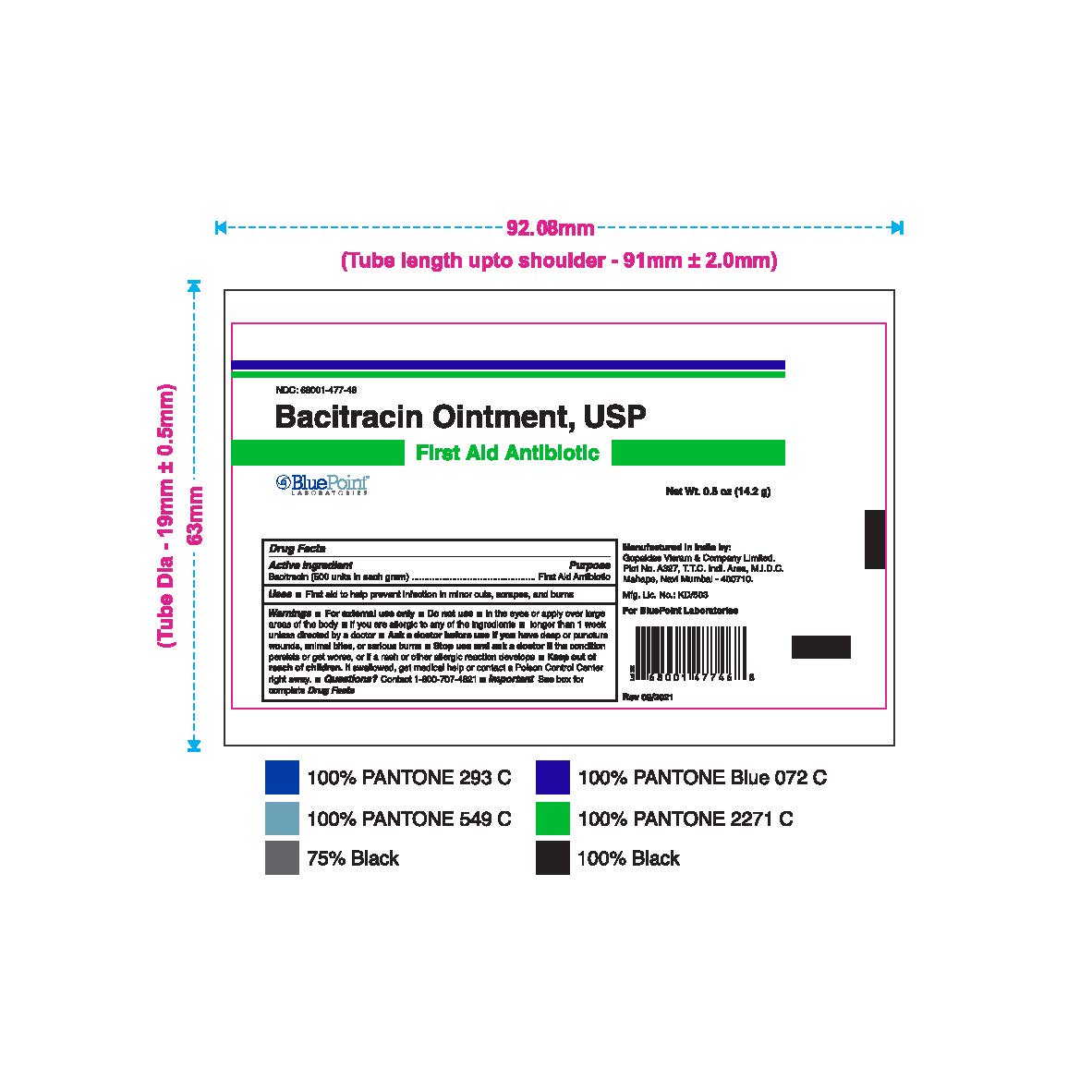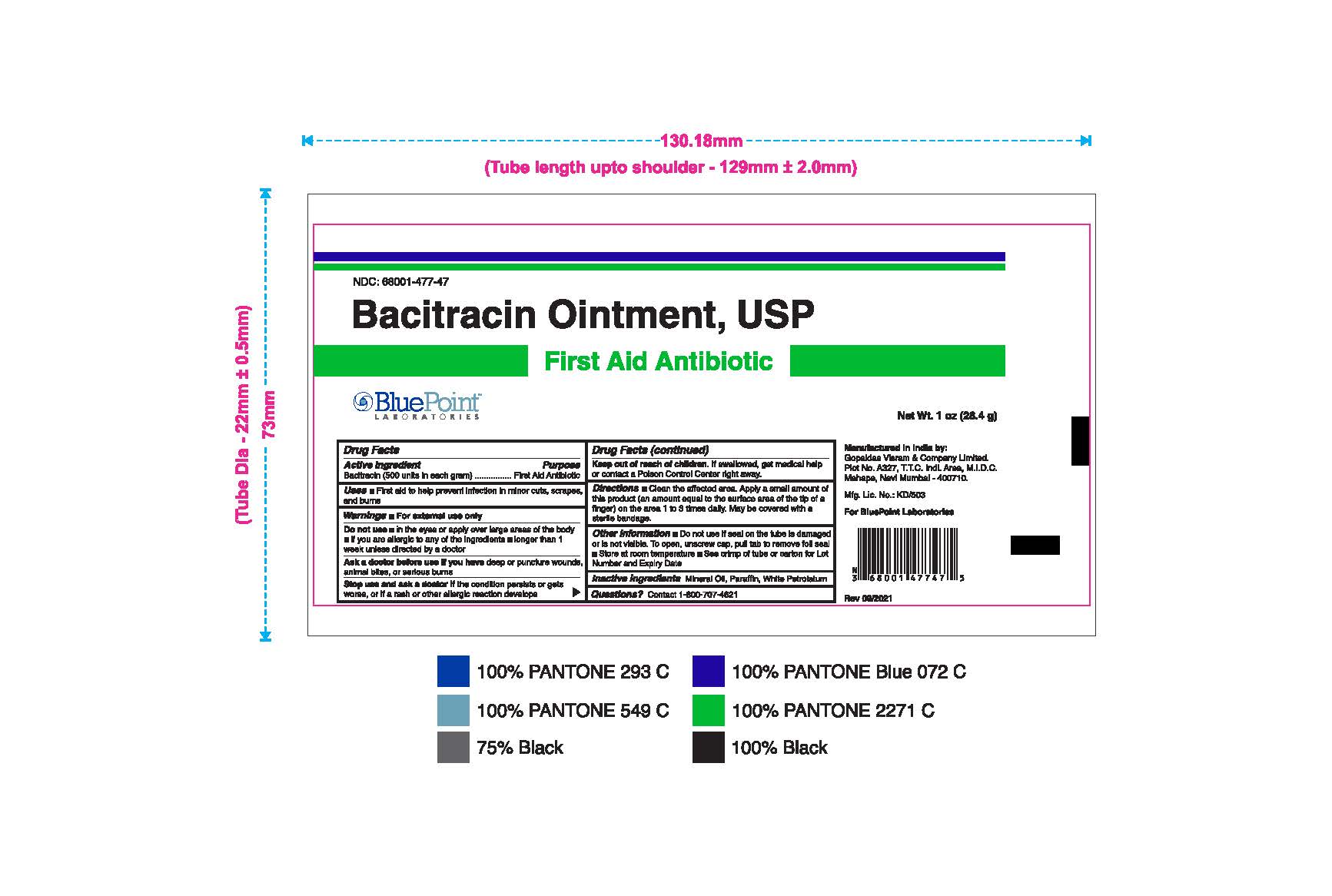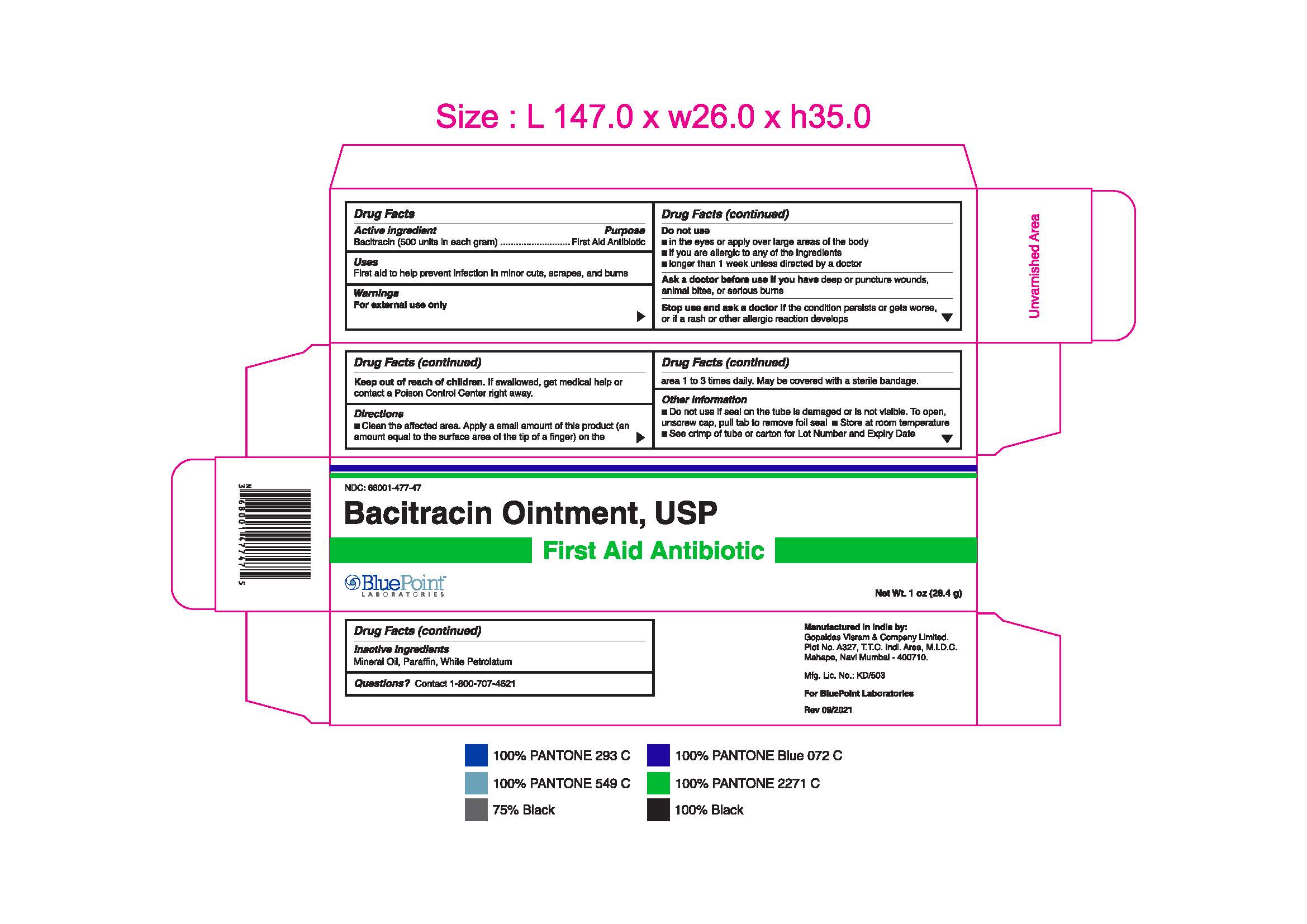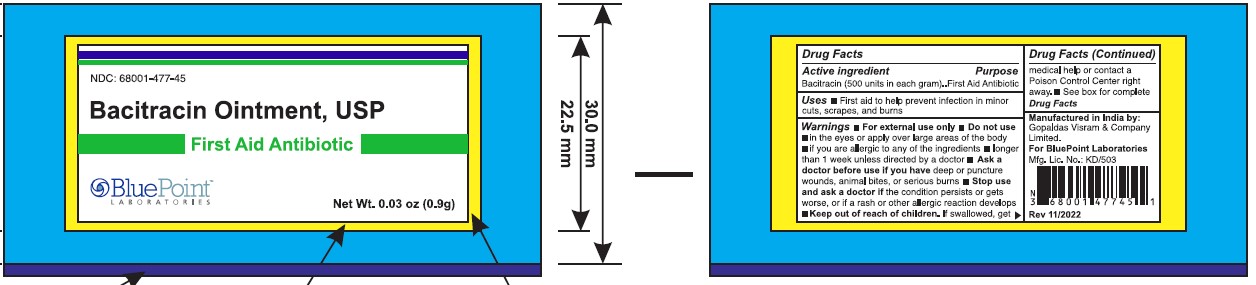 DRUG LABEL: Bacitracin
NDC: 68001-477 | Form: OINTMENT
Manufacturer: BluePoint Laboratories
Category: otc | Type: HUMAN OTC DRUG LABEL
Date: 20231117

ACTIVE INGREDIENTS: BACITRACIN 500 [iU]/1 g
INACTIVE INGREDIENTS: MINERAL OIL; PARAFFIN; WHITE PETROLATUM

Bacitracin_Ointment

Active ingredient

Bacitracin (500 Units in each gram)

Purpose

First Aid Antibiotic

Uses

- First aid to help prevent infection in minor cuts, scrapes and burns

Warnings

For external use only

Do not use

- in the eyes or apply over large areas of body
- if you are allergic to any of the ingredients
- longer than 1 week unless directed by a doctor

Ask a doctor before use if you have

deep or puncture wounds, animal bites, or serious burns

Stop use and ask a doctor if

the condition persists or gets worse, or if a rash or other allergic reaction develops.

Keep out of reach of children

If swallowed, get medical help or contact a Poison Control Centre right away.

Directions

Clean the affected area. Apply a small amount of this product (an amount equal to the surface area of the tip of a finger) on the area 1 to 3 times daily. May be covered with a sterile bandage.

Other information

- Do not use if seal on the tube is damaged or is not visible. To open, unscrew cap, pull tab to remove foil seal
- Store at room temperature
- See crimp of tube or carton for Lot Number and Expiry Date

Inactive Ingredients

Mineral Oil, Paraffin, White Petrolatum

Questions?

Contact- 1-800-707-4621

Manufactured in India by:

Gopaldas Visram & Company Limited,

Plot No. A327, T.T.C. Indl. Area, M.I.D.C.

Mahape, Navi Mumbai - 400710.

Mfg. Lic. No.: KD/503

For BluePoint Laboratories

Rev 09/2021

Principal Display Panel

Bacitracin sachet and carton 0.9g

PACKAGE LABEL

Bacitracin tube and carton 14.2g

PACKAGE LABEL

Bacitracin 28.4g tube and carton